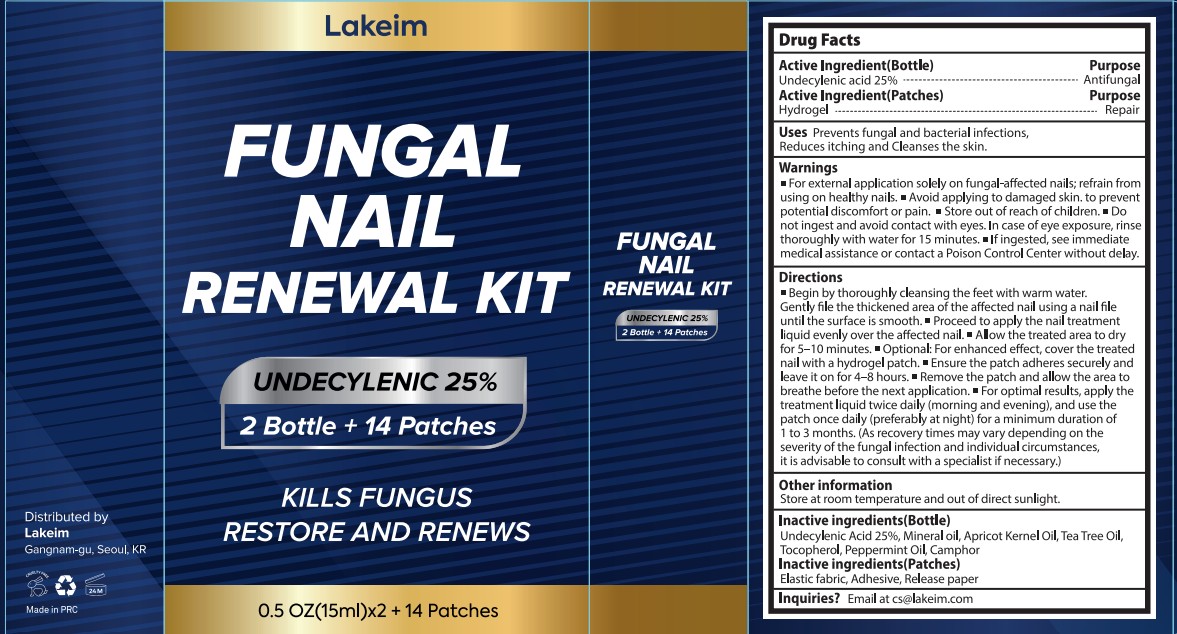 DRUG LABEL: Lakeim FUNGAL NAIL RENEWAL Kit
NDC: 87408-009 | Form: LIQUID
Manufacturer: Guangzhou Jingliang Cosmetics Co., Ltd.
Category: otc | Type: HUMAN OTC DRUG LABEL
Date: 20260222

ACTIVE INGREDIENTS: UNDECYLENIC ACID 25 g/100 mL
INACTIVE INGREDIENTS: PEPPERMINT OIL; CAMPHOR OIL; APRICOT KERNEL OIL; MINERAL OIL; TOCOPHEROL; TEA TREE OIL

Active Ingredient

Active ingredient: Undecylenic Acid 25%

Ask Doctor

if irritation or symptoms worsen or last for more than 4 weeks.

Do not use

• If you are pregnant or breastfeeding
• your skin is injured or cracked.
• you are under 18 years of age.
• irritation or discomfort occurs.
• you are using other medicines on your nails.

Keep Out Of Reach Of Children

If swallowed, get medical help or contact a poison control center right away.

Purpose

Antifungal

Stop Use

if irritation or symptoms worsen or last for more than 4 weeks.

When Using

• Do not apply to other parts of the body.
• Avoid making eye contact. In case of accidental eye contact, flush eyes with copious amounts of cold tap water.
• This product may not work for everyone.

Inactive ingredients

Mineral oil, Apricot Kernel Oil, Tea Tree Oil,Tocopherol, Peppermint Oil, Lavender Oil

Directions

Wash your feet thoroughly with warm water.

Gently smooth the thickened nail surface using a nail file until even.

Apply the nail treatment liquid evenly across the affected nail.

Make sure the treated area is fully dry before continuing.

For best results, use the treatment twice daily (morning and evening) for at least 1 to 3 months.

Since recovery time may differ depending on the severity of the fungal infection and individual conditions, consulting a specialist is recommended if needed.

Warnings

For external application solely on fungal-affected nails; refrain from using on healthy nails.

Avoid applying to damaged skin to prevent potential discomfort or pain.

Store out of reach of children.

Do not ingest and avoid contact with eyes.

In case of eye exposure, rinse thoroughly with water for 15 minutes.

If ingested, seek immediate medical assistance or contact a Poison Control Center without delay.

Uses

Prevents fungal and bacterial infections.

Reduces itching and cleanses the skin.

PACKAGE LABEL

Product Name: Lakeim FUNGAL NAIL RENEWAL KIT

Net Contents: 2x15ml (0.5 fl.oz.) Bottles